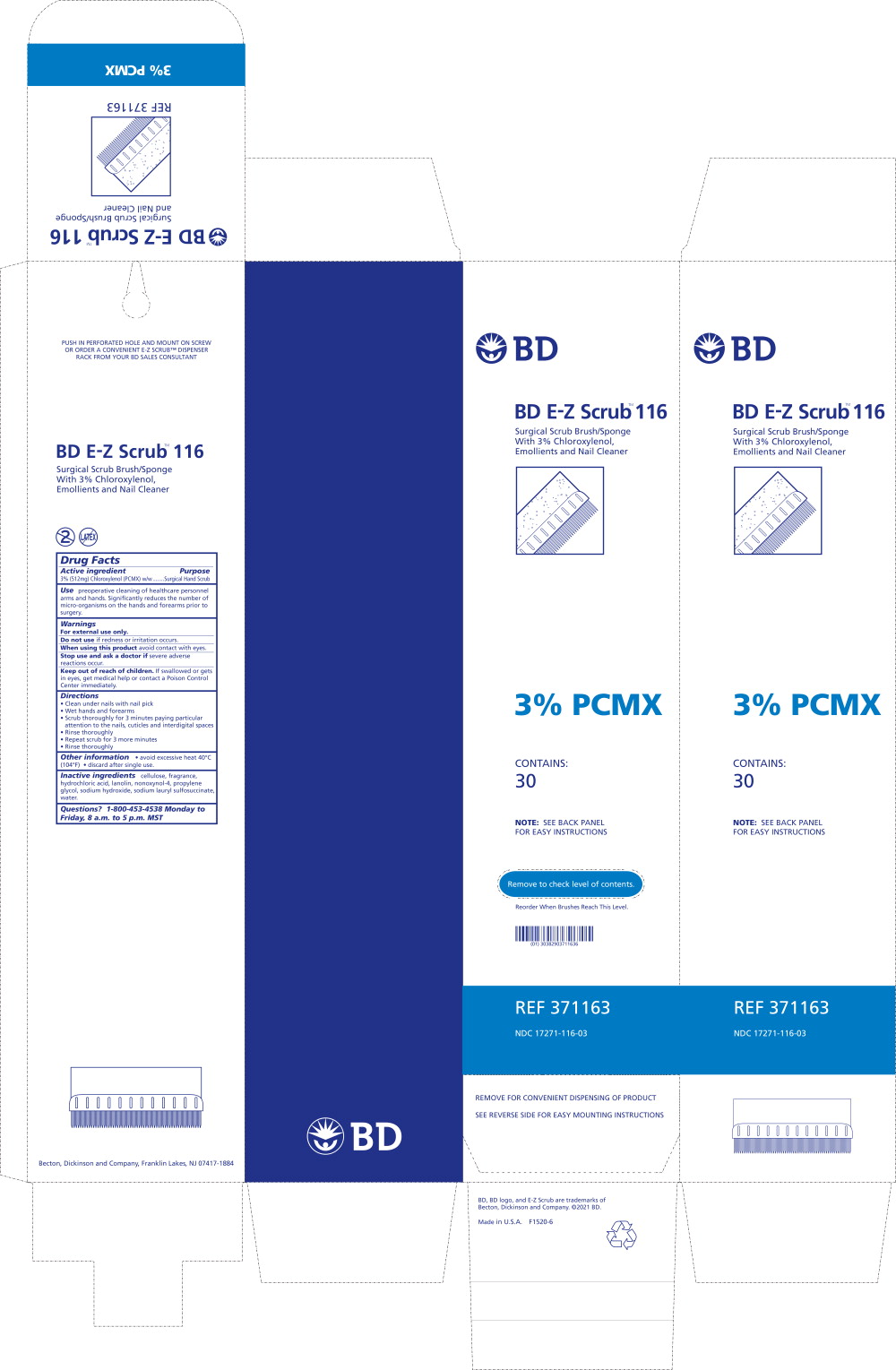 DRUG LABEL: BD E-Z SCRUB
NDC: 17271-116 | Form: SOLUTION
Manufacturer: Becton Dickinson and Company
Category: otc | Type: HUMAN OTC DRUG LABEL
Date: 20251208

ACTIVE INGREDIENTS: CHLOROXYLENOL
 30 mg/1 mL
INACTIVE INGREDIENTS: HYDROCHLORIC ACID; POWDERED CELLULOSE; LANOLIN; NONOXYNOL-4; PROPYLENE GLYCOL; SODIUM HYDROXIDE; DISODIUM LAURYL SULFOSUCCINATE; WATER

Drug Facts

Active ingredient

3% (512mg) Chloroxylenol (PCMX) w/w

Purpose

Surgical Hand Scrub

Use

preoperative cleaning of healthcare personnel arms and hands. Significantly reduces the number of micro-organisms on the hands and forearms prior to surgery.

Warnings

For external use only.

Do not use if redness or irritation occurs.

When using this product avoid contact with eyes.

Stop use and ask a doctor if severe adverse reactions occur.

Keep out of reach of children. If swallowed or gets in eyes, get medical help or contact a Poison Control Center immediately.

Directions

- Clean under nails with nail pick
- Wet hands and forearms
- Scrub thoroughly for 3 minutes paying particular attention to the nails, cuticles and interdigital spaces
- Rinse thoroughly
- Repeat scrub for 3 more minutes
- Rinse thoroughly

Other information

- avoid excessive heat 40°C (104°F)
- discard after single use.

Inactive ingredients

cellulose, fragrance, hydrochloric acid, lanolin, nonoxynol-4, propylene glycol, sodium hydroxide, sodium lauryl sulfosuccinate, water.

Questions?

1-800-453-4538 Monday to Friday, 8 a.m. to 5 p.m. MST

Principal Display Panel – Carton Label

BD

BD E-Z Scrub™ 116

Surgical Scrub Brush/Sponge
With 3% Chloroxylenol,
Emollients and Nail Cleaner

3% PCMX

CONTAINS:
30

NOTE: SEE BACK PANEL
FOR EASY INSTRUCTIONS

Remove to check level of contents

Reorder When Brushes Reach This Level.

REF 371163

NDC 17271-116-03

REMOVE FOR CONVENIENT DISPENSING OF PRODUCT SEE REVERSE SIDE FOR EASY MOUNTING INSTRUCTIONS